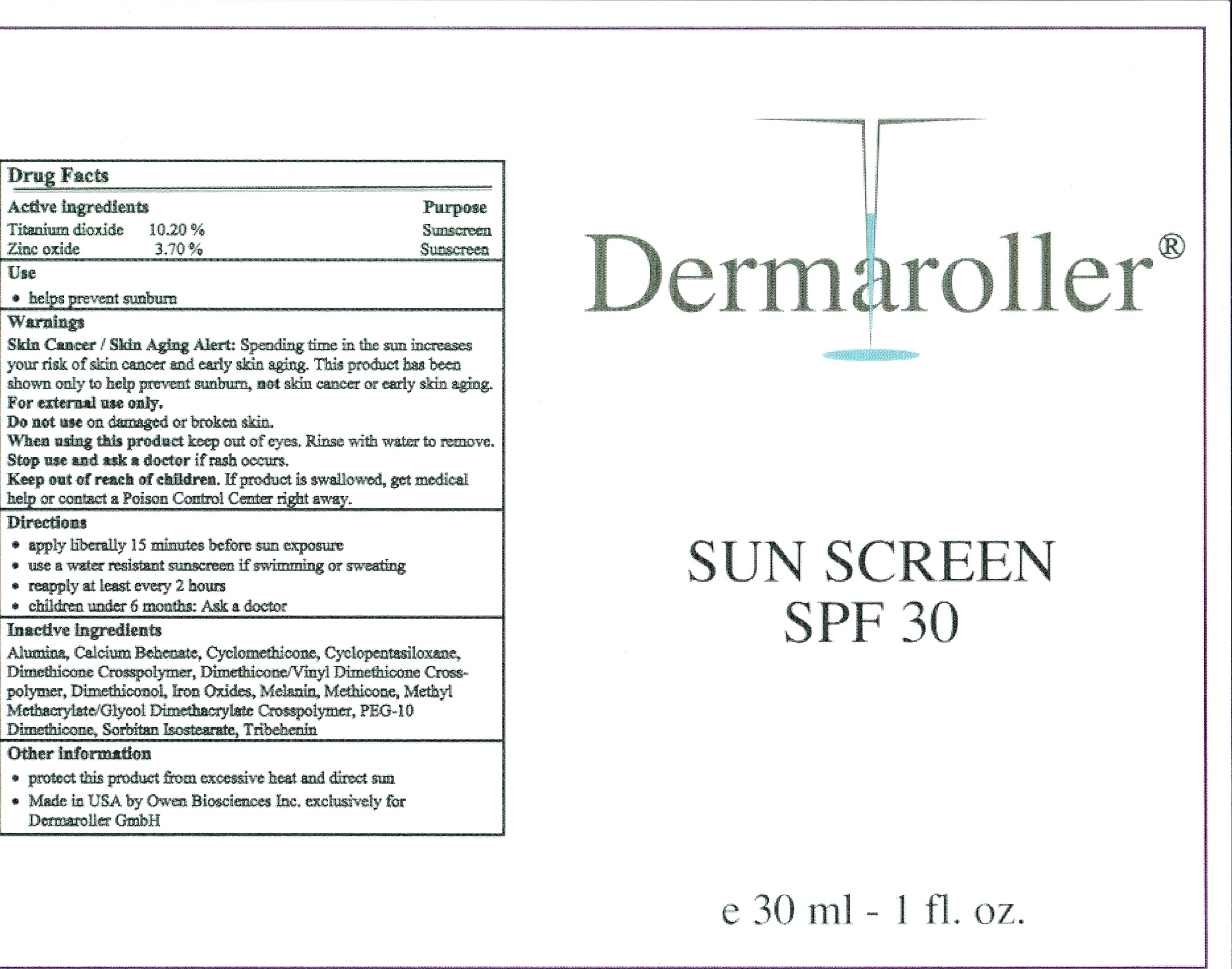 DRUG LABEL: Dermaroller Anhydrous Sunscreen
NDC: 59958-201 | Form: CREAM
Manufacturer: Owen Biosciences, Inc.
Category: otc | Type: HUMAN OTC DRUG LABEL
Date: 20250110

ACTIVE INGREDIENTS: TITANIUM DIOXIDE 10.2 g/100 g; ZINC OXIDE 3.7 g/100 g
INACTIVE INGREDIENTS: CYCLOMETHICONE 17.5 g/100 g; TRIBEHENIN 1 g/100 g; FERRIC OXIDE RED 0.09 g/100 g; FERRIC OXIDE YELLOW 0.25 g/100 g; FERROSOFERRIC OXIDE 0.01 g/100 g

Dermaroller Anhydrous Sunscreen

Drug Facts

Active ingredients Purpose

Titanium Dioxide 10.20% Sunscreen

Zinc Oxide 3.70% Sunscreen

USES

Helps Prevent sunburn.

Higher SPF gives more sunburn protection

Provides moderate protection against sunburn.

Warnings

For external use only. When using this product

keep out of eyes. Rinse with water to remove.

Stop use and ask doctor if rash and irritation

develops and lasts. Keep out of reach of

children. If swallowed, get medical help or

contact poison control center right away.

Directions

Apply evenly before sun exposure and as

needed. For children under 6 months of age: ask

a doctor. Reapply as needed or after towel

drying, swimming or perspiring.

Other Information

Sun alert: Limiting sun exposure, wearing protective clothing, and using sunscreens may reduce the risk of skin cancer, and other

harmful effects of the sun.

Inactive Ingredients

Cyclopentasiloxane, Cyclomethicone, Dimethicone Crosspolymer, Methyl Methacrylate/Glycol Dimethacrylate Crosspolymer,

Dimethicone/Vinyl Dimethicone Crosspolymer, Melanin, Tribehenin, Calcium Behenate, Sorbitan Isostearate, Dimethiconol,

Alumina, PEG-10 Dimethicone, Methicone, Iron Oxides.

Dosage & Admiinistration

- apply liberally 15 minutes before sun exposure

- use water resistant sunscreen if swimming or sweating

- reapply at least every 2 hours

- children under 6 months: Ask a doctor

Keep out of reach of children. If product is swallowed, get medical help or contact Poison Control Center right away.